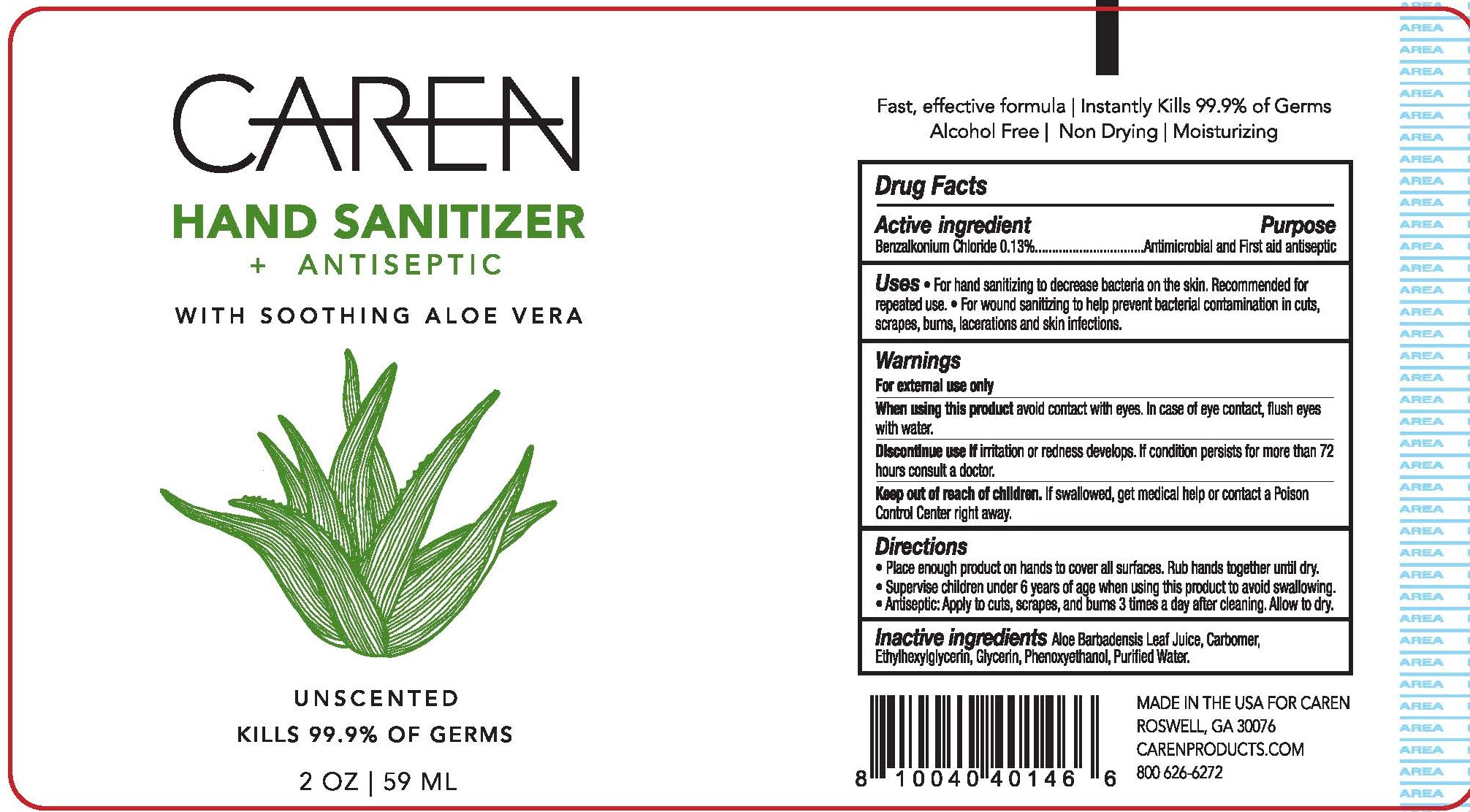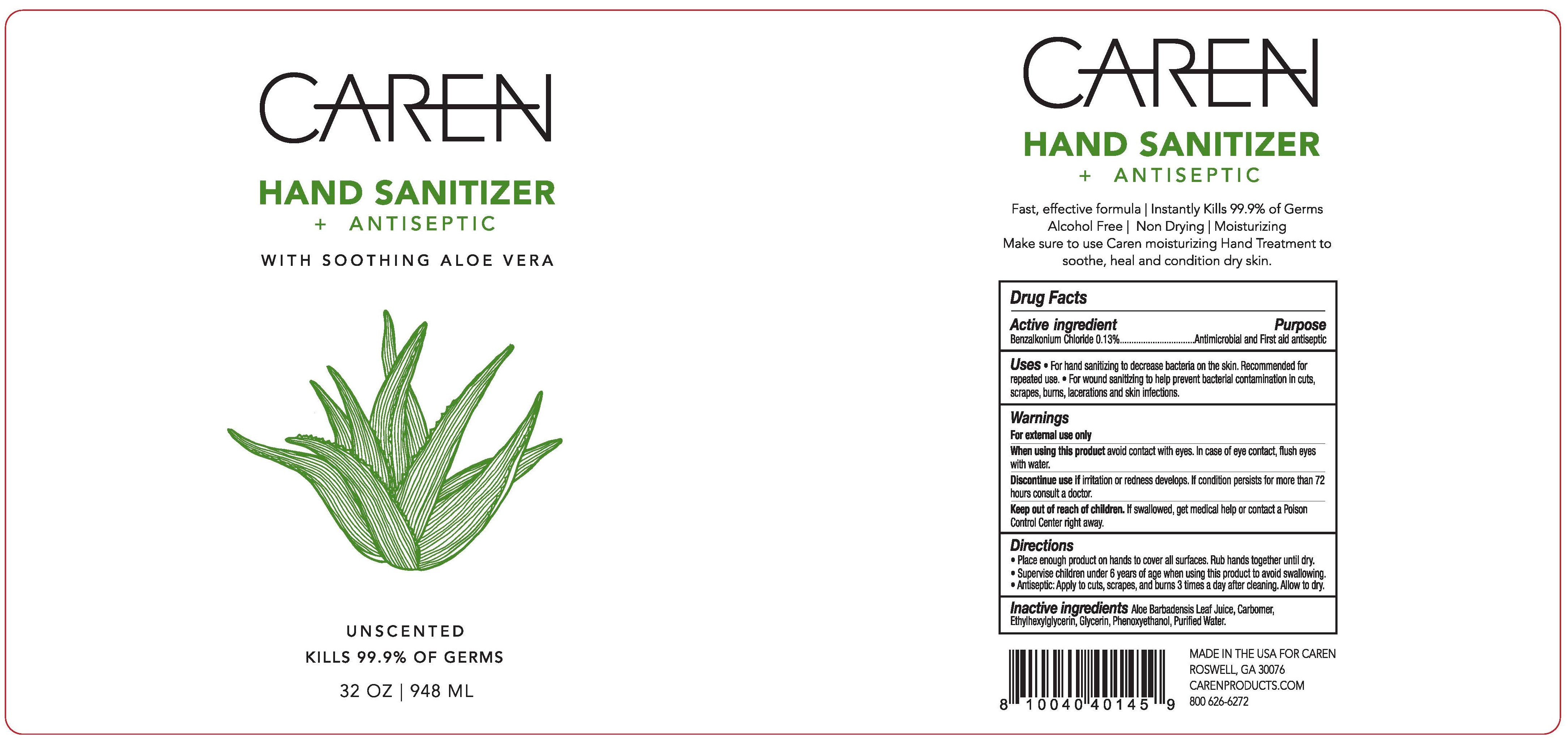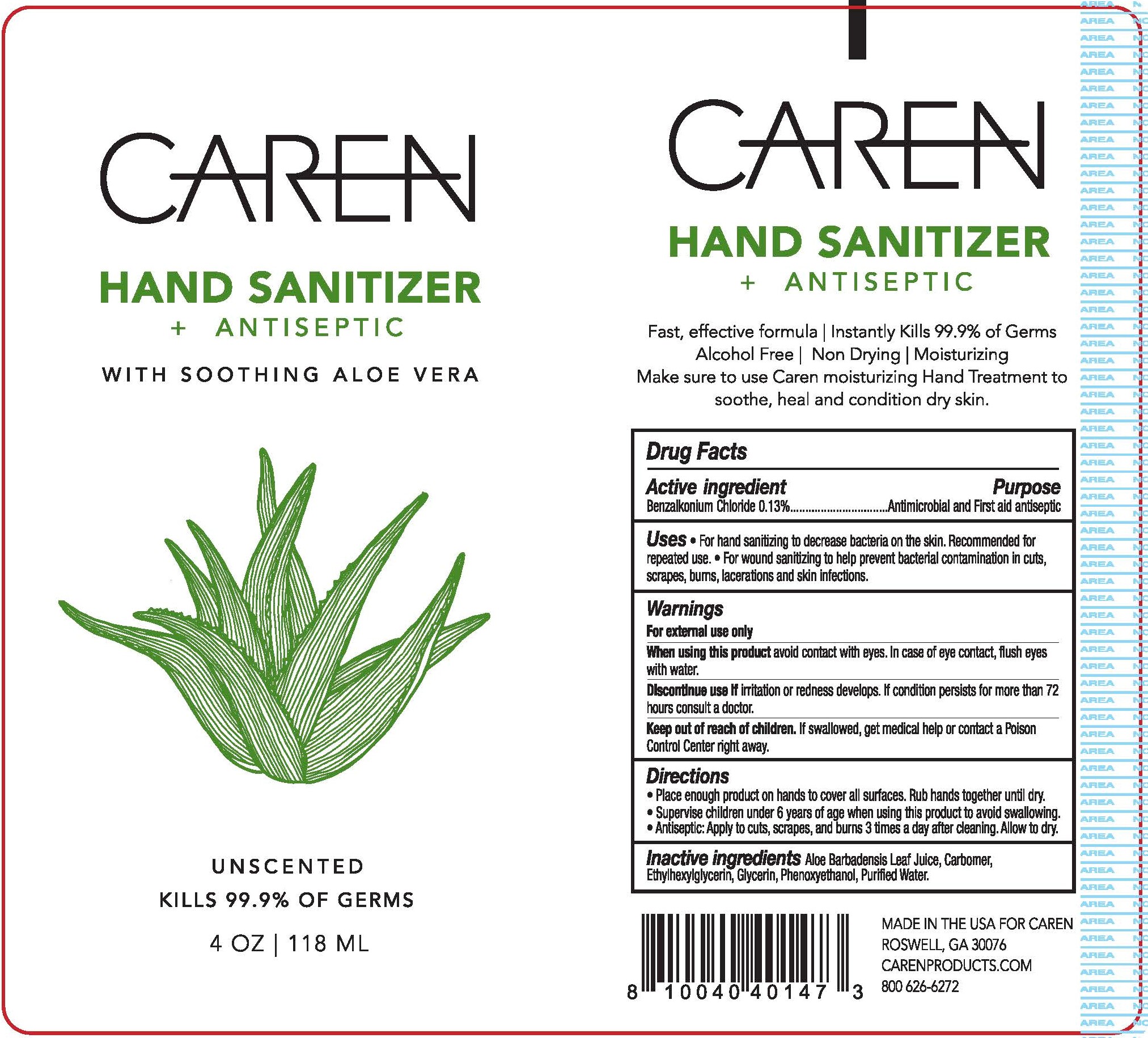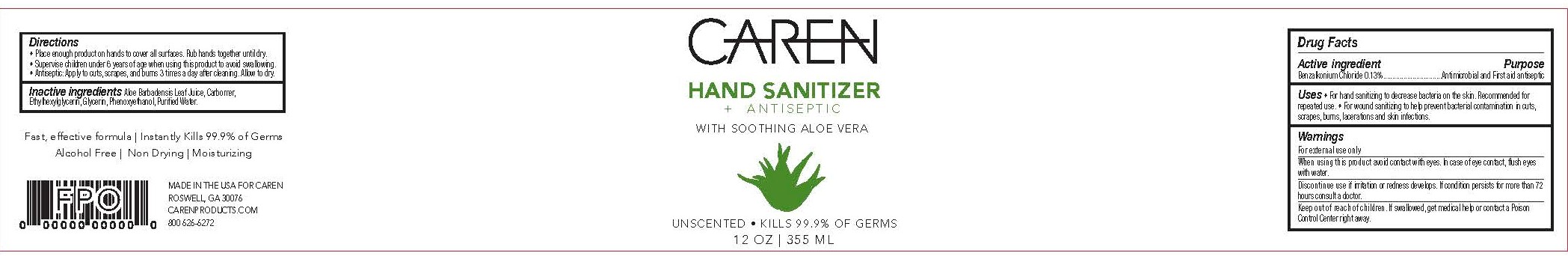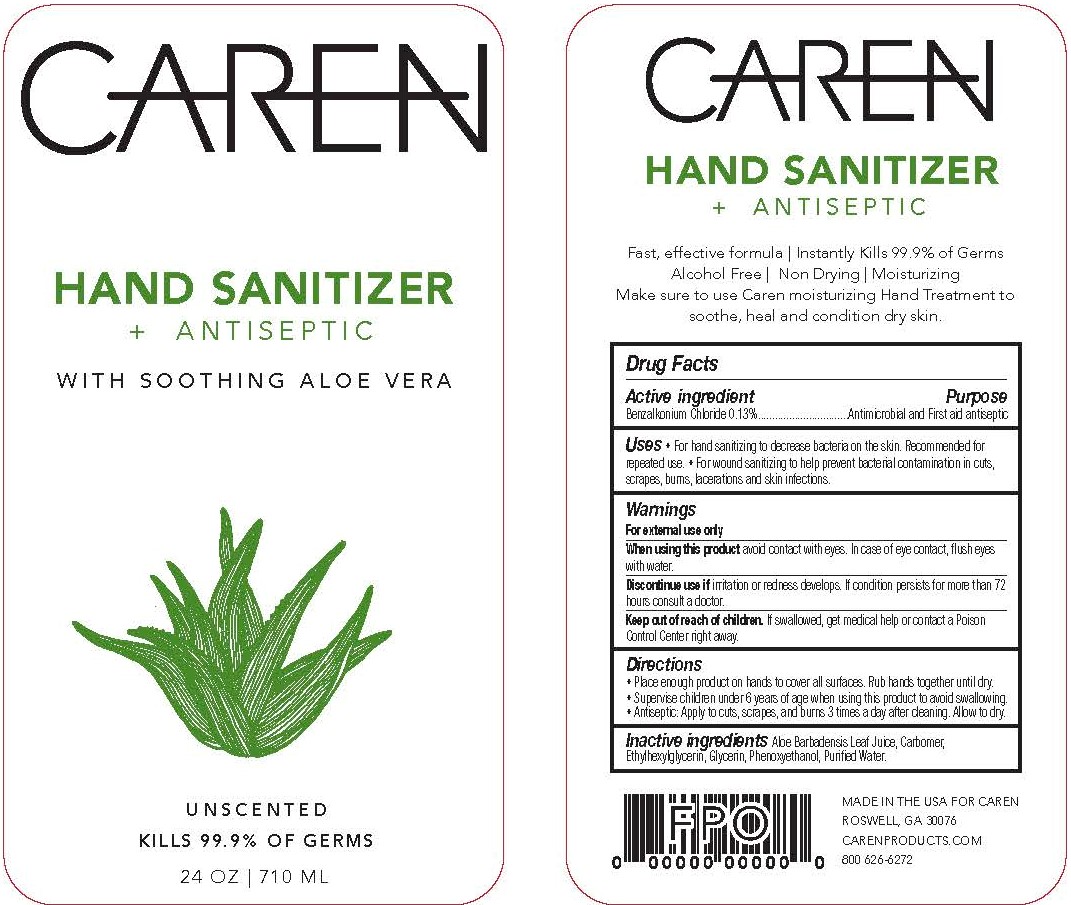 DRUG LABEL: Caren Hand Sanitizer  Antiseptic
NDC: 77009-0420 | Form: GEL
Manufacturer: Caren Products, LLC
Category: otc | Type: HUMAN OTC DRUG LABEL
Date: 20200924

ACTIVE INGREDIENTS: BENZALKONIUM CHLORIDE 0.0013 kg/1 kg
INACTIVE INGREDIENTS: GLYCERIN; CARBOMER HOMOPOLYMER, UNSPECIFIED TYPE; WATER; SODIUM HYDROXIDE; ALOE; PHENOXYETHANOL; ETHYLHEXYLGLYCERIN

Active Ingredient(s)

Benzalkonium Chloride....................Purpose: Antimicrobial and First Aid Antiseptic

Purpose

Antimicrobial and First Aid Antiseptic

Uses

- For hand sanitizing to decrease bacteria on the skin. Recommended for repeated use.
- For wound sanitizing to help prevent bacterial contamination in cuts, scrapes, burns, lacerations, and sking infections.

Warnings

For external use only.

When using this product avoid contact with eyes. In case of eye contact, flush eyes with water.

STOP USE

Discontinue use if irratation or redness develops. If condition persists for more than 72 hours consult a doctor.

Keep out of reach of children. If swallowed, get medical help or contact a Poison Control Center right away.

Directions

- Place enough product on hands to cover all surfaces. Rub hands together until dry.
- Supervise children under 6 years of age when using this product to avoid swallowing.
- Antiseptic: Apply to cuts, scrapes, and burns 3 times a day after cleaning. Allow to dry.

Inactive ingredients

Aloe, Carbomer, Ethylhexylglycerin, Glycerin, Phenoxyethanol, Purified Water